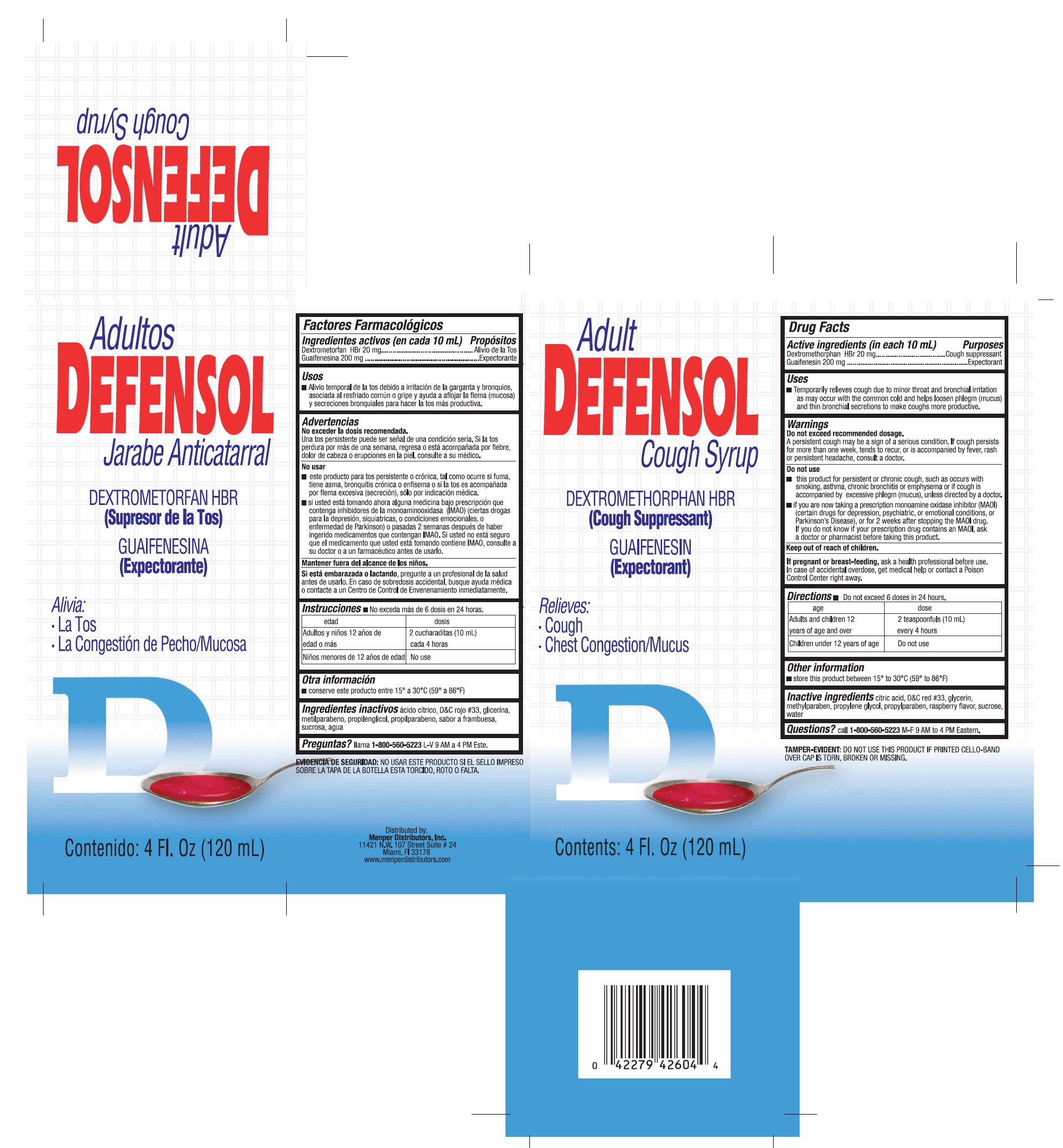 DRUG LABEL: Defensol Adult Syrup
NDC: 53145-039 | Form: LIQUID
Manufacturer: Menper Distributors, Inc.
Category: otc | Type: HUMAN OTC DRUG LABEL
Date: 20250722

ACTIVE INGREDIENTS: GUAIFENESIN 200 mg/10 mL; DEXTROMETHORPHAN HYDROBROMIDE 20 mg/10 mL
INACTIVE INGREDIENTS: CITRIC ACID ACETATE; D&C RED NO. 33; GLYCERIN; METHYLPARABEN; PROPYLENE GLYCOL; PROPYLPARABEN; RASPBERRY; SUCROSE; WATER

Defensol Adult Syrup

Active ingredients (in each 10mL tsp)

Dextromethorphan HBr 20 mg……………………Cough suppressant

Guaifenesin 200 mg………………………………Expectorant

Purposes

Cough Suppressant

Expectorant

Uses

Temporarily relieves cough due to minor throat and bronchial irritation as may occur with the common cold and helps loosen phlegm (mucus) and thin brochial secretions to make cougs more productive.

Warnings

Do not exceed recommended dosage.

A persistent cough may be a sign of a serious condition. If cough persists more than one week, tends to recur, or is accompanied by fever, rash, or persistent headache, consult a doctor.

Do not use:

- This product for persistent or chronic cough, such as occurs with smoking, asthma, chronic bronchitis or emphysema or if cough is accompanied by excessive phlegm (mucus), unless directed by a doctor.
- if you are now taking a prescription monoamine oxidase inhibitor (MAOI) (certain drugs for depression, psychiatric or emotional conditions, or Parkinson’s disease), or for 2 weeks after stopping the MAOI drug. If you do not know if your prescription drug contains an MAOI, ask a doctor or pharmacist before taking this product.

Keep out of reach of children.

If you are pregnant or breast-feeding,

ask a health professional before use.

In case of accidental overdose, get medical help or contact a Poison Control Center right away.

Directions:Do not exceed 6 doses in 24 hours.

age | dose
Adults and children12 years of age and over | 2 teaspoonfuls (10 mL) every 4 hours
Children under 12 years of age | Do not use

Other information

- Store this product between 15°-30°C (59°-86°F)

Inactive ingredients

citric acid, D&C red #33, glycerin, methylparaben, propylene glycol, propylparaben ,raspberry flavor, sucrose,water,

Question?

call 1-800-560-5223 M-F 9 AM- 4PM Eastern